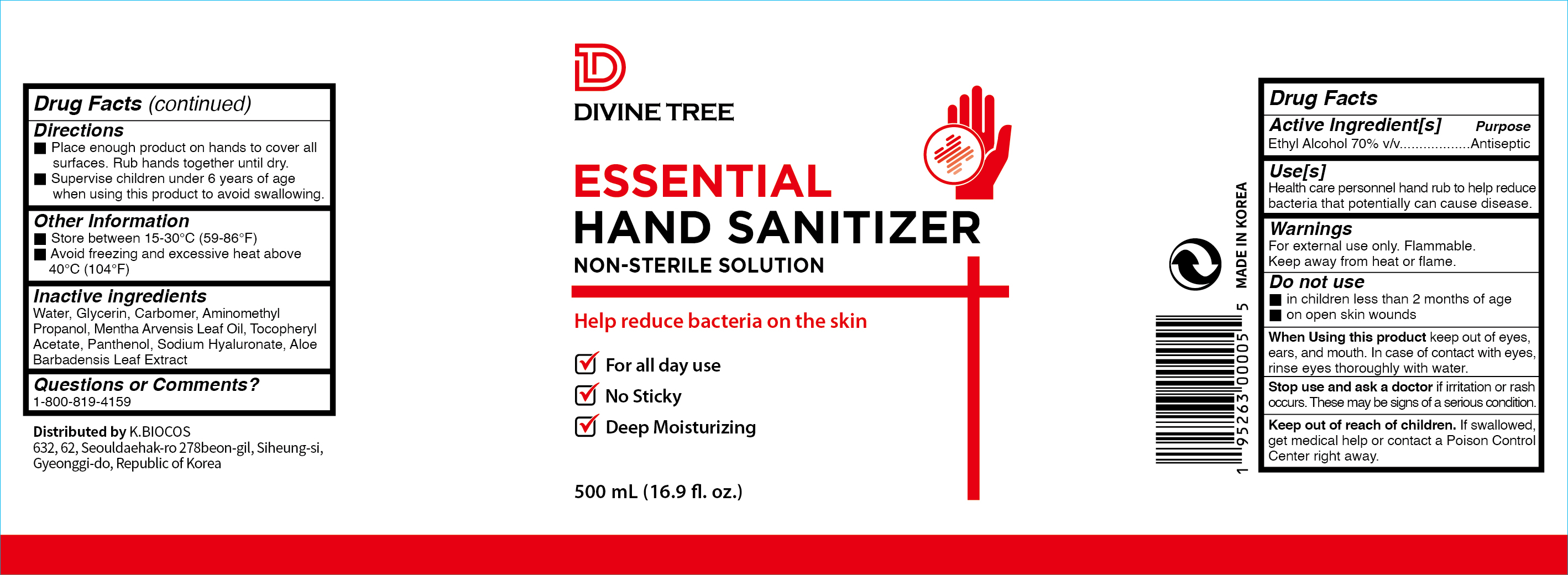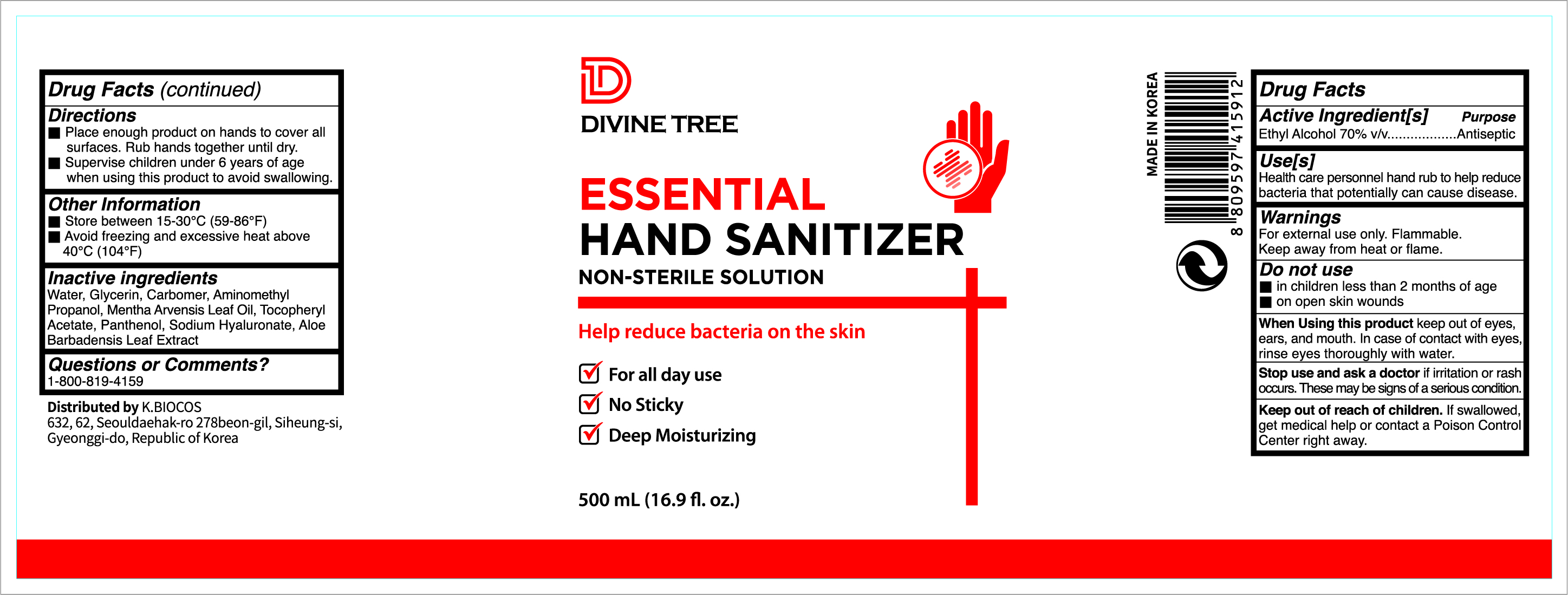 DRUG LABEL: Divine Tree Hand Sanitizer Gel
NDC: 73494-500 | Form: LIQUID
Manufacturer: K.BIOCOS
Category: otc | Type: HUMAN OTC DRUG LABEL
Date: 20200604

ACTIVE INGREDIENTS: ALCOHOL 70 mL/100 mL
INACTIVE INGREDIENTS: ALOE VERA LEAF; MENTHA ARVENSIS LEAF OIL; HYALURONATE SODIUM; PANTHENOL; GLYCERIN; CARBOMER 940; AMINOMETHYLPROPANOL; WATER; .ALPHA.-TOCOPHEROL ACETATE

Divine Tree Hand Sanitizer Gel 500ml

Active Ingredient

Ethyl Alcohol 70% v/v. Purpose Antiseptic

Purpose(s)

Purpose-Antiseptic

Use(s)

Health care personnel hand rub to help reduce bacteria that potentially can cause disease.

Warnings

For external use only. Flammable. Keep away from heat or flame

Do not use

- In children less than 2 months of age
- on open skin wounds

When Using This Product keep out of eyes, ears, and mouth. In case of contact with eyes, rinse eyes thoroughly with water.

Stop Use and Ask a Doctor if irritation or rash occurs. These may be signs of a serious condition.

Keep Out Of Reach Of Children if swallowed, get medical help or contact a Poison Control Center right away.

Directions

- Place enough product on hands to cover all surfaces. Rub hands together until dry.
- Supervise children under 6 years of age when using this product to avoid swallowing.

Other Information

- Store between 15-30℃ (59-86℉)
- Avoid freezing and excessive heat above 40℃ (104℉)

Inactive Ingredients

Inactive Ingredients-Water, Glycerin, Carbomer, Aminomethyl Propanol, Mentha Arvensis Leaf Oil, Tocopheryl Acetate, Panthenol, Sodium Hyaluronate, Aloe Barbadensis Leaf Extract

Questions Or Comments-1-800-819-4159

Pakage Label - Principal Display Panel

Divine Tree
Hand Sanitizer Gel
Non-Sterile Solution
Help Reduce Bacteria on the skin

- For All Day Use
- No Sticky
- Deep Moisturizing

500ml 16.9 fl.oz